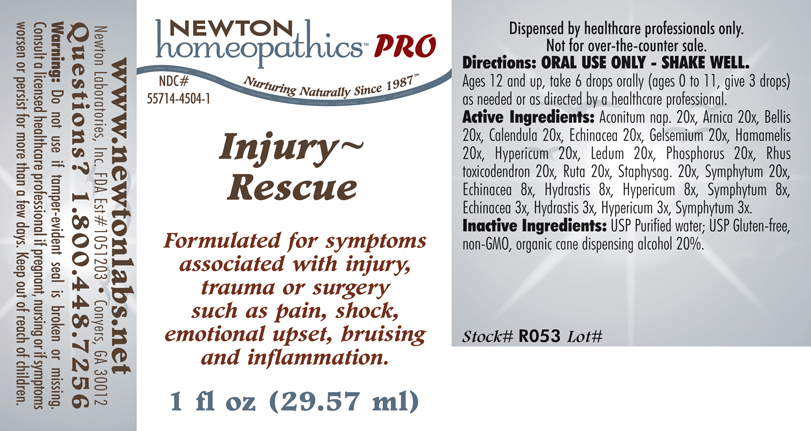 DRUG LABEL: Injury - Rescue 
NDC: 55714-4504 | Form: LIQUID
Manufacturer: Newton Laboratories, Inc.
Category: homeopathic | Type: HUMAN PRESCRIPTION DRUG LABEL
Date: 20110601

ACTIVE INGREDIENTS: Aconitum Napellus 20 [hp_M]/1 mL; Arnica Montana 20 [hp_X]/1 mL; Bellis Perennis 20 [hp_X]/1 mL; Calendula Officinalis Flowering Top 20 [hp_X]/1 mL; Echinacea, Unspecified 20 [hp_X]/1 mL; Gelsemium Sempervirens Root 20 [hp_X]/1 mL; Hamamelis Virginiana Root Bark/stem Bark 20 [hp_X]/1 mL; Hypericum Perforatum 20 [hp_X]/1 mL; Ledum Palustre Twig 20 [hp_X]/1 mL; Phosphorus 20 [hp_X]/1 mL; Toxicodendron Pubescens Leaf 20 [hp_X]/1 mL; Ruta Graveolens Flowering Top 20 [hp_X]/1 mL; Delphinium Staphisagria Seed 20 [hp_X]/1 mL; Comfrey Root 20 [hp_X]/1 mL; Goldenseal 8 [hp_X]/1 mL
INACTIVE INGREDIENTS: Alcohol

Injury - Rescue

INDICATIONS & USAGE SECTION

Injury - Rescue Formulated for symptoms associated with injury, trauma or surgery such as pain, shock, emotional upset, bruising and inflammation.

DOSAGE & ADMINISTRATION SECTION

Directions: ORAL USE ONLY - SHAKE WELL. Ages 12 and up, take 6 drops orally (ages 0 to 11, give 3 drops) as needed or as directed by a healthcare professional.

ACTIVE INGREDIENT SECTION

Aconitum nap. 20x, Arnica 20x, Bellis 20x, Calendula 20x, Echinacea 20x, Gelsemium 20x, Hamamelis 20x, Hypericum 20x, Ledum 20x, Phosphorus 20x, Rhus toxicodendron 20x, Ruta 20x, Staphysag. 20x, Symphytum 20x, Echinacea 8x, Hydrastis 8x, Hypericum 8x, Symphytum 8x, Echinacea 3x, Hydrastis 3x, Hypericum 3x, Symphytum 3x.

PURPOSE SECTION

Formulated for symptoms associated with injury, trauma or surgery such as pain, shock, emotional upset, bruising and inflammation.

INACTIVE INGREDIENT SECTION

Inactive Ingredients: USP Purified Water; USP Gluten-free, non-GMO, organic cane dispensing alcohol 20%.

QUESTIONS? SECTION

www.newtonlabs.net Newton Laboratories, Inc. FDA Est # 1051203 - Conyers, GA 30012
Questions? 1.800.448.7256

WARNINGS SECTION

Warning: Do not use if tamper - evident seal is broken or missing. Consult a licensed healthcare professional if pregnant, nursing or if symptoms worsen or persist for more than a few days. Keep out of reach of children.

PREGNANCY OR BREAST FEEDING SECTION

Consult a licensed healthcare professional if pregnant or nursing or if symptoms worsen or persist for more than a few days.

KEEP OUT OF REACH OF CHILDREN SECTION

Keep out of reach of children.